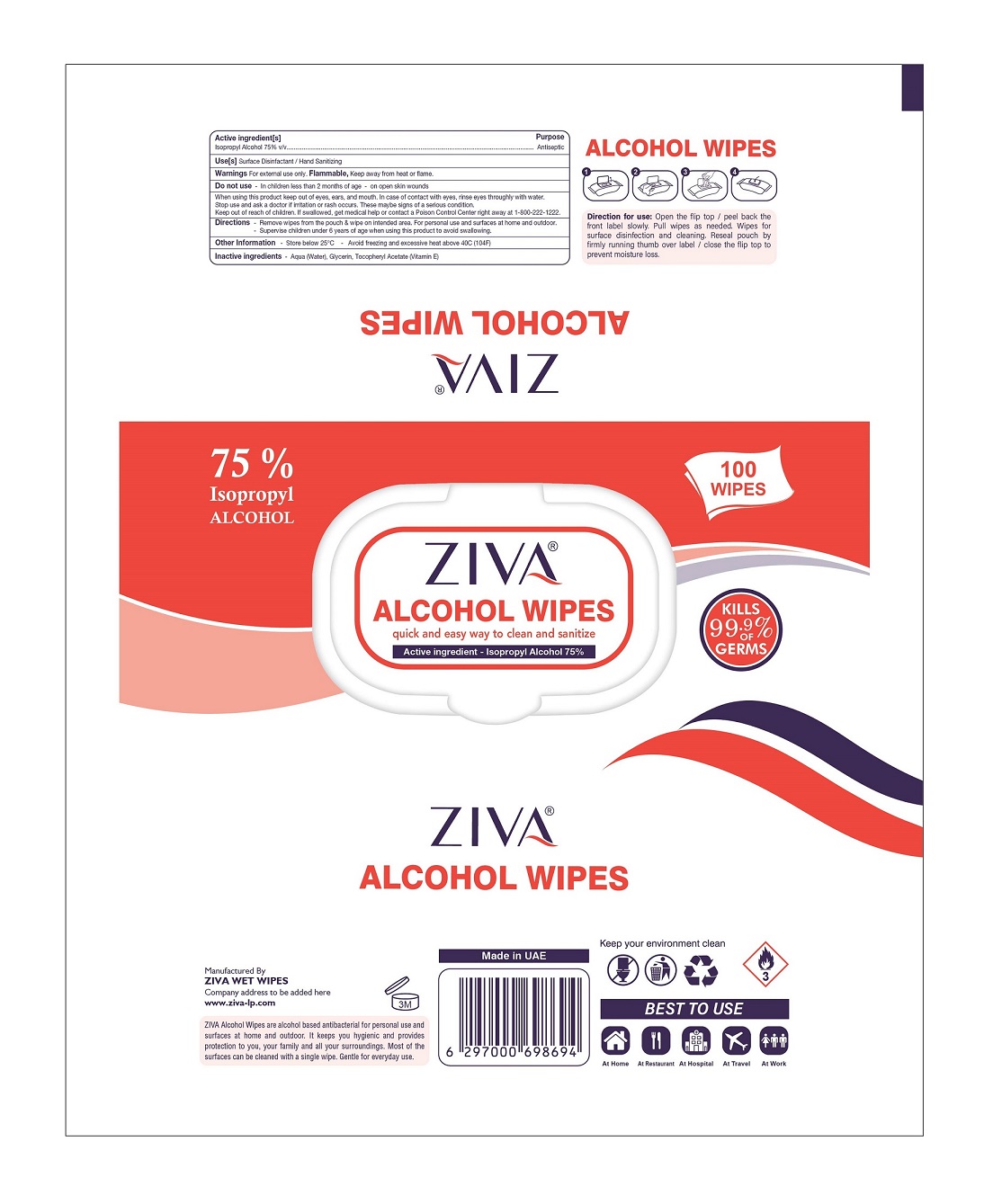 DRUG LABEL: ZIVA ALCOHOL WIPES
NDC: 81450-008 | Form: CLOTH
Manufacturer: Ziva Wetwipes FZCo
Category: otc | Type: HUMAN OTC DRUG LABEL
Date: 20231005

ACTIVE INGREDIENTS: ISOPROPYL ALCOHOL 75 mL/100 mL
INACTIVE INGREDIENTS: WATER; GLYCERIN; .ALPHA.-TOCOPHEROL ACETATE

Drug Facts

Active Ingredient(s)

Isopropyl Alcohol 75% v/v

Purpose

Antiseptic

Use(s)

Surface Disinfactant / Hand Sanitizing

Warnings

Warnings For External use only. Flammable Keep away from heat or flame

Do not use - In children less than 2 months of age – on open skin wounds.

When using this product keep out of eyes, ears and mouth, In case of contact with eyes, rinse eyes thoroughly with water.
Stop use and ask a doctor if irritation or rash occurs. These maybe signs of a serious condition.
Keep out of reach of children. If swallowed, get medical help or contact a poison control center right away at 1-800-222-1222.

Directions

Remove wipes from the pouch & wipe on intended area. For personal use and surfaces at home and outdoor.
Supervise children under 6 years of age when using this product to avoid swallowing.

Other information

Store below 25°C – Avoid freezing and excessive heat above 40°C (104°F)

Inactive Ingredients

Aqua (Water), Glycerin, Tocopheryl Acetate (Vitamin E)